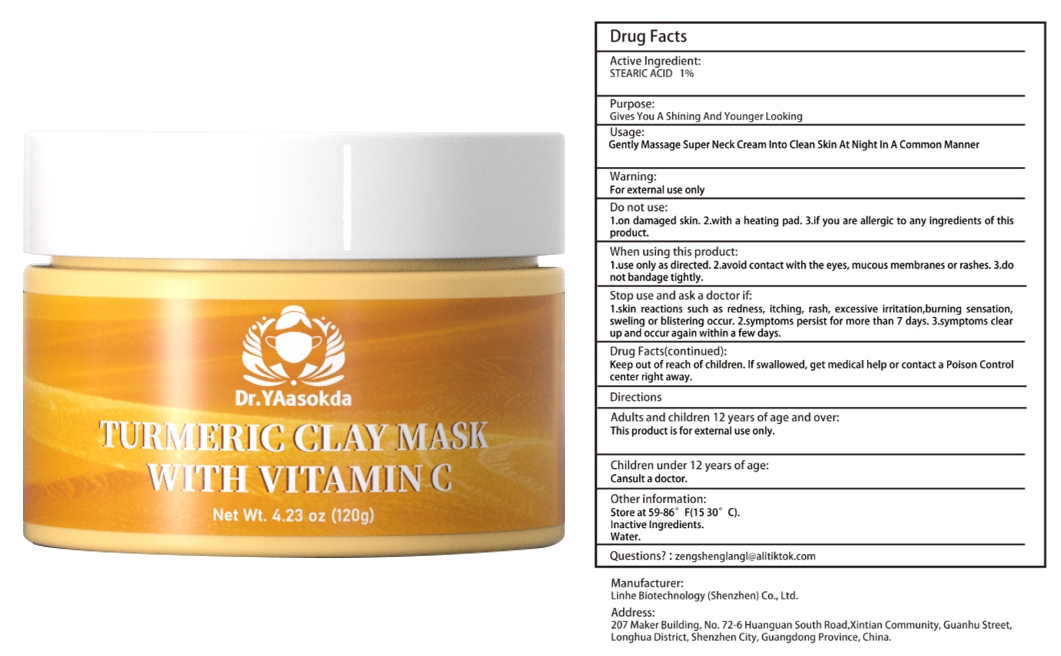 DRUG LABEL: Turmeric Mud Film Vitamin C
NDC: 84575-070 | Form: LIQUID
Manufacturer: Linhe Biotechnology (Shenzhen) Co., Ltd
Category: otc | Type: HUMAN OTC DRUG LABEL
Date: 20241211

ACTIVE INGREDIENTS: STEARIC ACID 1.2 g/120 g
INACTIVE INGREDIENTS: GLYCERIN

Turmeric Mud Film Vitamin C

ACTIVE INGREDIENT

STEARIC ACID 1%

PURPOSE

Gives You A Shining And Younger Looking

INDICATIONS AND USAGE

Gently Massage Super Neck Cream Into Clean Skin At Night In A Common Manner

WARNINGS

For external use only.

Patients with renal failure and those with low heart rates should not use this product. This product is notintended to diagnose,treat, cure or prevent any disease.

DOSAGE AND ADMINISTRATION

Take this product and spray it on the glans and coronal sulcus. Spray 1-2 times each time to avoid the urethral opening.

INACTIVE INGREDIENT

WATER

STORAGE AND HANDLING

Store in a cool and dark place away from light

Keep out of reach of children,in case of overdose, get medical help or contact a PoisonControl Center right away.